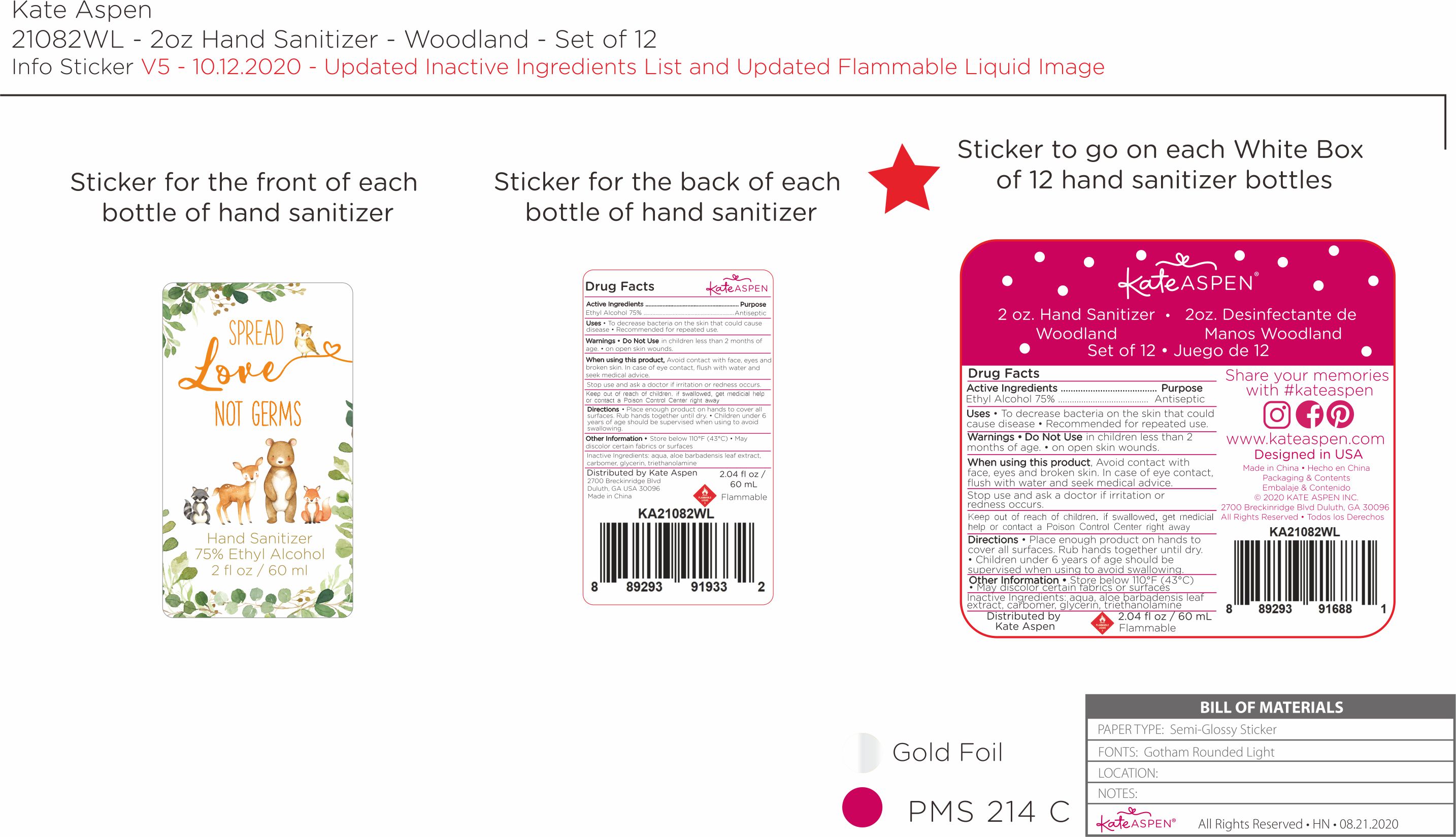 DRUG LABEL: Kate Aspen Spread Love Not Germs Hand Sanitizer Woodland 75 Ethyl Alcohol
NDC: 81091-000 | Form: GEL
Manufacturer: Kate Aspen, Inc.
Category: otc | Type: HUMAN OTC DRUG LABEL
Date: 20230223

ACTIVE INGREDIENTS: ALCOHOL 0.75 mL/1 mL
INACTIVE INGREDIENTS: WATER; ALOE VERA LEAF; CARBOMER HOMOPOLYMER, UNSPECIFIED TYPE; GLYCERIN; TROLAMINE

Kate Aspen Spread Love Not Germs Hand Sanitizer Woodland 75 Ethyl Alcohol

Active Ingredients

Ethyl Alcohol 75%

Purpose

Antiseptic

Uses

• To decrease bacteria on the skin that could cause disease • Recommended for repeated use.

Warnings

Do Not Use

• in children less than 2 months of age. • on open skin wounds.

When using this product,

Avoid contact with face, eyes and broken skin. In case of eye contact, flush with water and seek medical advice.

Stop use and ask a doctor

if irritation or redness occurs.

Keep out of reach of children. If swallowed, get medical help or contact a Poison Control Center right away

Directions

• Place enough product on hands to cover all surfaces. Rub hands together until dry. • Children under 6 years of age should be supervised when using to avoid swallowing.

Other Information

• Store below 110°F (43°C)
• May discolor certain fabrics or surfaces

Inactive Ingredients:

aqua, aloe barbadensis leaf extract, carbomer, glycerin, triethanolamine